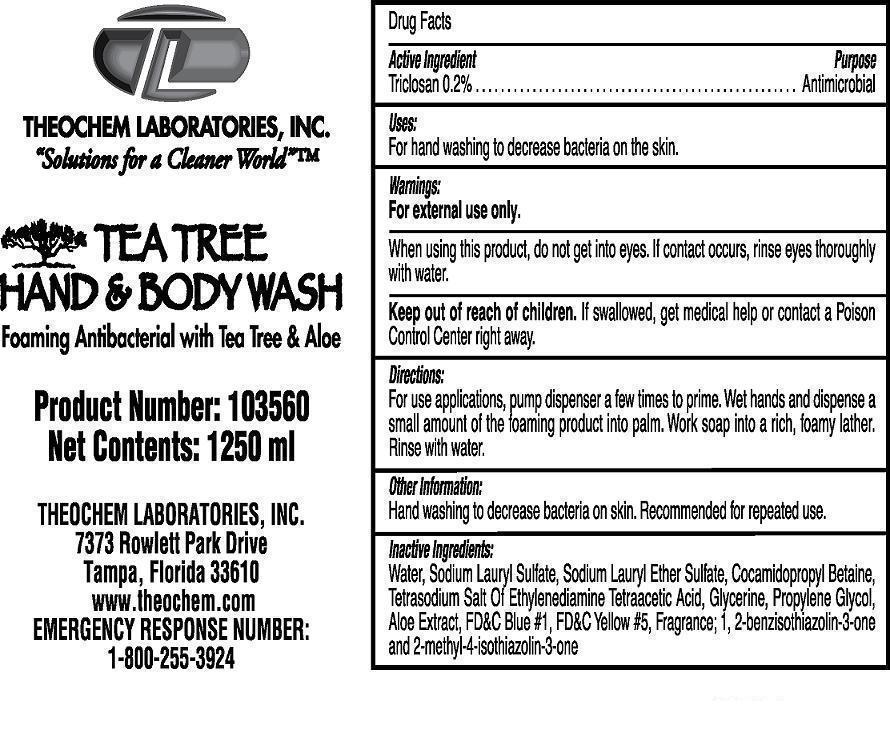 DRUG LABEL: Theochem Tea Tree Hand and Body Wash
NDC: 68878-140 | Form: SOAP
Manufacturer: Theochem Laboratories Inc
Category: otc | Type: HUMAN OTC DRUG LABEL
Date: 20131008

ACTIVE INGREDIENTS: TRICLOSAN 0.002 g/1 mL
INACTIVE INGREDIENTS: WATER

Tea Tree Hand and Body Wash

Active Ingredient

Triclosan 0.2%

Purpose:

Antimicrobial

Uses:

For hand washing to decrease bacteria on the skin.

Warnings:

For external use only.

When using this product, do not get into eyes. If contact occurs, rinse eyes thoroughly with water.

Keep out of reach of children.

If swallowed, get medical help or contact a Poison Control Center right away.

Directions:

For use applications, pump dispenser a few times to prime. Wet hands and dispense a small amount of the foamimg product into palm.

Work soap into a rich, foamy lather. Rinse with water.

Other Information:

Hand washing to decrease bacteria on skin. Recommended for repeated use.

Inactive Ingredients:

Water, Sodium Lauryl Sulfate, Sodium Lauryl Ether Sulfate, Cocamidopropyl Betaine, Tetrasodium Salt of Ehylenediamine Tetraacetic Acid, Glycerine, Propylene Glycol, Aloe Extract, FD&C Blue # 1, FD&C Yellow # 5, Fragrance, 1, 2-benzisothiazolin-3-one and 2-methyl-4-isothiazolin-3-one